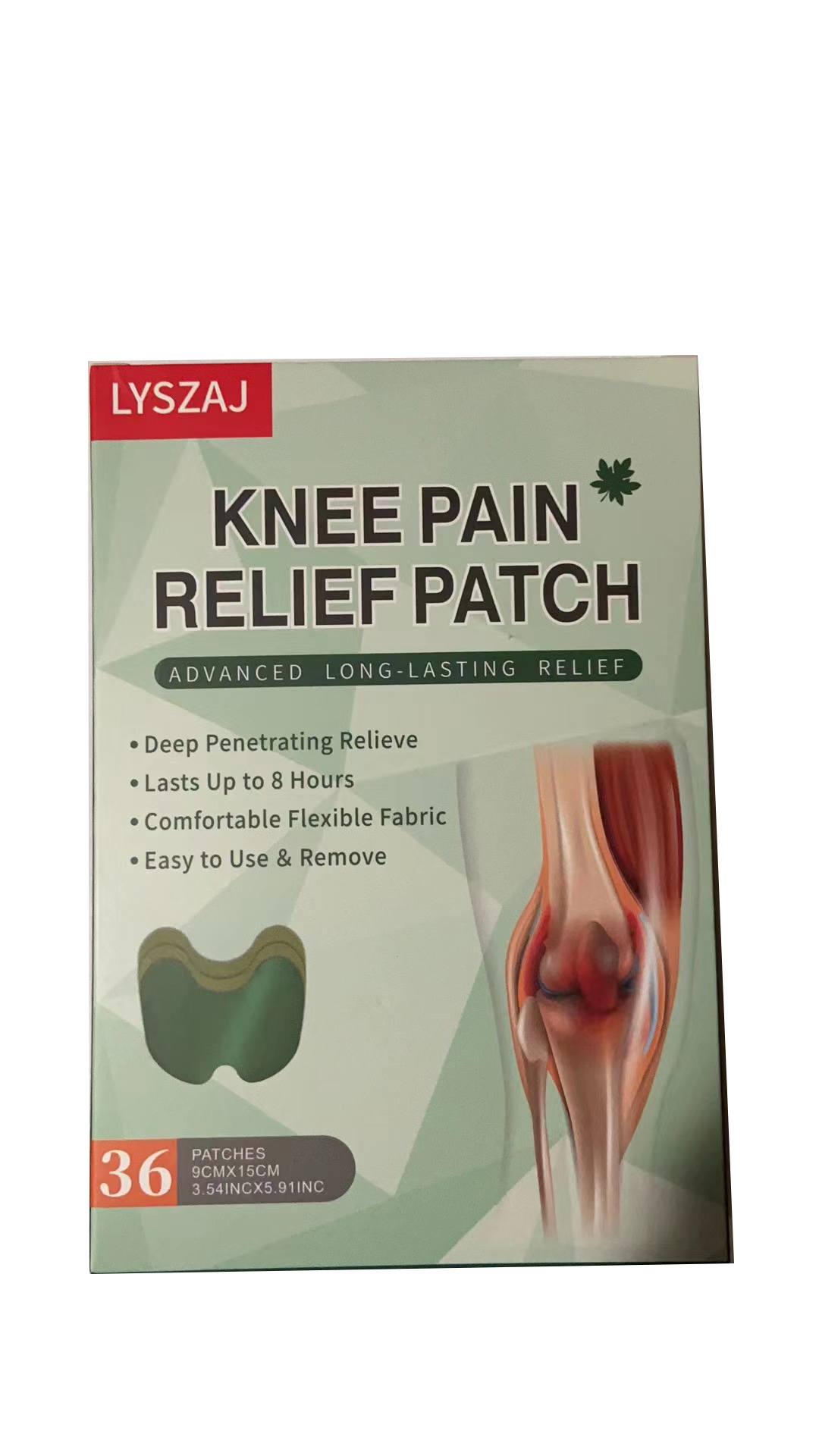 DRUG LABEL: relief patch
NDC: 84727-021 | Form: OINTMENT
Manufacturer: Guangzhou Baishili Trading Co., Ltd
Category: otc | Type: HUMAN OTC DRUG LABEL
Date: 20240923

ACTIVE INGREDIENTS: BORNEOL 100 mg/100 mg

ACTIVE INGREDIENT

BORNEOL 25%

CAMPHOR 20%

Health care function

Relieve neck, shoulder, waist, leg pain and promote health.

Usage

Opened the package back lining paper torn off,clean your skin where the discomfort,aim at the knee or discomfort parts were applied,the corresponding around six to eight hours per post.

Matters needing attention

1. The skin lesions were banned, allergic to wormwood careful.

2. During the period of a few people use local have tickling feeling or a red rash,does not affect theuse disappeared gradually after stopping.
3. The use of skin burns is a normal phenomenon.

Unsuitable people

Pregnant women, those allergic to wormwood are prohibited.

Keep out of reach of children.

If swallowed, get medical help or contact a Poison Control Center right away.

DOSAGE & ADMINISTRATION SECTION

Apply one piece at a time, and each piece should be applied for 8 hours

INACTIVE INGREDIENT SECTION

menthol 55%

Dosage & administration section

BORNEOL 25%
CAMPHOR 20%

MENTHOL 55%

Usage: Opened the package back lining paper torn off,clean your skin where the discomfort,aimat the knee or discomfort parts were applied,the corresponding around six to eight hours per post.